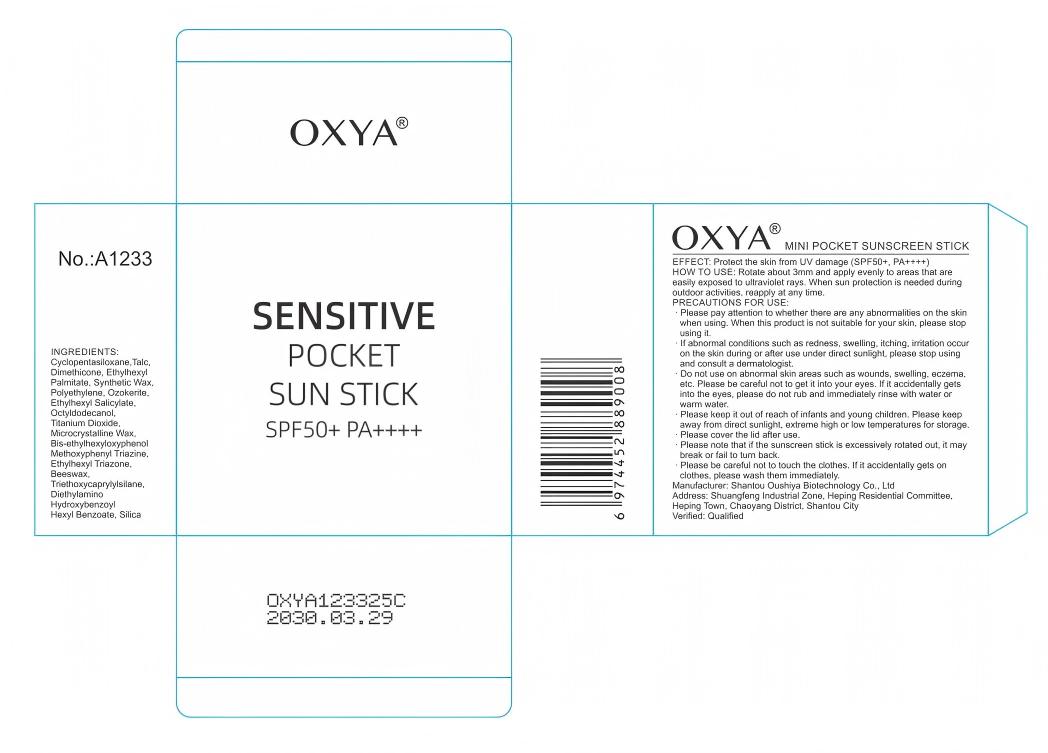 DRUG LABEL: SENSITIVE POCKET SUN
NDC: 85819-771 | Form: STICK
Manufacturer: Shantou Oushiya Biotechnology Co., Ltd
Category: homeopathic | Type: HUMAN OTC DRUG LABEL
Date: 20250614

ACTIVE INGREDIENTS: TALC 15 mg/1 1; CYCLOPENTASILOXANE 26.5 mg/1 1
INACTIVE INGREDIENTS: ETHYLHEXYL TRIAZONE; POLYETHYLENE; DIMETHICONE; MICROCRYSTALLINE WAX; TRIETHOXYCAPRYLYLSILANE; SODIUM POTASSIUM ALUMINUM SILICATE; OCTYLDODECANOL; BIS-ETHYLHEXYLOXYPHENOL METHOXYPHENYL TRIAZINE; DIETHYLAMINO HYDROXYBENZOYL HEXYL BENZOATE; SYNTHETIC WAX (540 MW); ETHYLHEXYL SALICYLATE; TITANIUM DIOXIDE; ETHYLHEXYL PALMITATE; BEESWAX

WARNINGS

Please keep it out of reach of infants and young children

KEEP OUT OF REACH OF CHILDREN SECTION

INDICATIONS AND USAGE

Rotate about 3mm and apply evenly to areas that are easily exposed to ultraviolet rays.

PURPOSE

Protect the skin from UV damage

DOSAGE AND ADMINISTRATION

SPF50+,PA++++

ACTIVE INGREDIENT

CYCLOPENTASILOXANE,TALC,

INACTIVE INGREDIENT

TRIETHOXYCAPRYLYLSILANE,DIMETHICONE,ETHYLHEXYL PALMITATE,SYNTHETIC WAX,POLYETHYLENE,ETHYLHEXYL SALICYLATE,TITANIUM DIOXIDE,SILICA,DIMETHICONE,MICROCRYSTALLINE WAX,BEESWAX,OCTYLDODECANOL,ETHYLHEXYL TRIAZONE,BIS-ETHYLHEXYLOXYPHENOL METHOXYPHENYL TRIAZINE,DIETHYLAMINO HYDROXYBENZOYL HEXYL BENZOATE